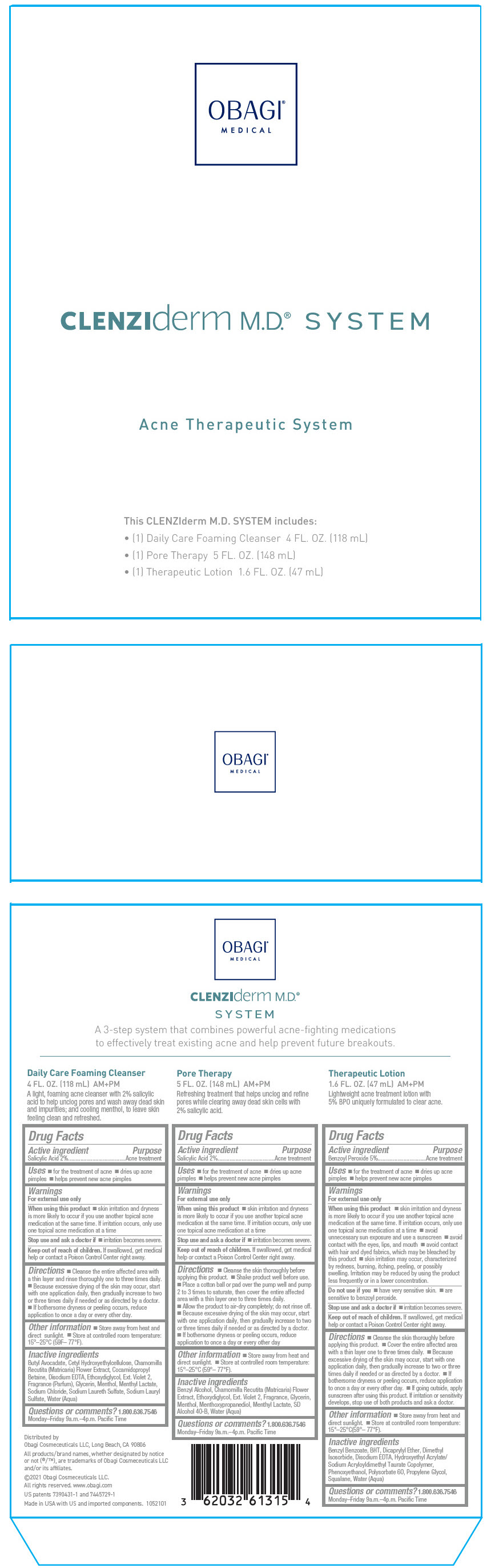 DRUG LABEL: clenziderm m.d. system
NDC: 62032-613 | Form: KIT | Route: TOPICAL
Manufacturer: Obagi Cosmeceuticals LLC
Category: otc | Type: HUMAN OTC DRUG LABEL
Date: 20250319

ACTIVE INGREDIENTS: SALICYLIC ACID 20 mg/1 mL; SALICYLIC ACID 20 mg/1 mL; BENZOYL PEROXIDE 50 mg/1 mL
INACTIVE INGREDIENTS: SODIUM LAURETH-3 SULFATE; SODIUM LAURYL SULFATE; COCAMIDOPROPYL BETAINE; CETYL HYDROXYETHYLCELLULOSE (350000 MW); EDETATE DISODIUM; MENTHOL, UNSPECIFIED FORM; MENTHYL LACTATE, (-)-; EXT. D&C VIOLET NO. 2; WATER; BUTYL AVOCADATE; DIETHYLENE GLYCOL MONOETHYL ETHER; CHAMOMILE; GLYCERIN; SODIUM CHLORIDE; ALCOHOL; DIETHYLENE GLYCOL MONOETHYL ETHER; BENZYL ALCOHOL; 3-((L-MENTHYL)OXY)PROPANE-1,2-DIOL; GLYCERIN; MENTHOL, UNSPECIFIED FORM; MENTHYL LACTATE, (-)-; EXT. D&C VIOLET NO. 2; WATER; CHAMOMILE; BENZYL BENZOATE; DICAPRYLYL ETHER; HYDROXYETHYL ACRYLATE/SODIUM ACRYLOYLDIMETHYL TAURATE COPOLYMER (100000 MPA.S AT 1.5%); PROPYLENE GLYCOL; SQUALANE; POLYSORBATE 60; DIMETHYL ISOSORBIDE; PHENOXYETHANOL; EDETATE DISODIUM; BUTYLATED HYDROXYTOLUENE; WATER

CLENZIDERM M.D.™ SYSTEM
ACNE THERAPEUTIC SYSTEM

Drug Facts

Active ingredient

Salicylic Acid 2%

Purpose

Acne treatment

Uses

- for the treatment of acne
- dries up acne pimples
- helps prevent new acne pimples

Warnings

For external use only

When using this product

- skin irritation and dryness is more likely to occur if you use another topical acne medication at the same time. If irritation occurs, only use one topical acne medication at a time.

Stop use and ask a doctor if

- irritation becomes severe.

Keep out of reach of children. If swallowed, get medical help or contact a Poison Control Center right away.

Directions

- Cleanse the entire affected area with a thin layer and rinse thoroughly one to three times daily.
- Because excessive drying of the skin may occur, start with one application daily, then gradually increase to two or three times daily if needed or as directed by a doctor.
- If bothersome dryness or peeling occurs, reduce application to once a day or every other day.

Other information

- Store away from heat and direct sunlight.
- Store at controlled room temperature: 15°C–25°C (59°F– 77°F).

Inactive ingredients

Benzyl Benzoate, BHT, Dicaprylyl Ether, Dimethyl Isosorbide, Disodium EDTA, Hydroxyethyl Acrylate/ Sodium Acryloyldimethyl Taurate Copolymer, Phenoxyethanol, Polysorbate 60, Propylene Glycol, Squalane, Water (Aqua)

Questions or comments?

1.800.636.7546

Monday–Friday 9a.m.–4p.m. Pacific Time

Drug Facts

Active ingredient

Salicylic acid 2%

Purpose

Acne treatment

Uses

- for the treatment of acne
- dries up acne pimples
- helps prevent new acne pimples

Warnings

For external use only

When using this product

- skin irritation and dryness is more likely to occur if you use another topical acne medication at the same time. If irritation occurs, only use one topical acne medication at a time.

Stop use and ask a doctor if

- irritation becomes severe.

Keep out of reach of children. If swallowed, get medical help or contact a Poison Control Center right away.

Directions

- Cleanse the skin thoroughly before applying this product.
- Shake product well before use.
- Place a cotton ball or pad over the pump well and pump 2 to 3 times to saturate, then cover the entire affected area with a thin layer one to three times daily.
- Allow the product to air-dry completely; do not rinse off.
- Because excessive drying of the skin may occur, start with one application daily, then gradually increase to two or three times daily if needed or as directed by a doctor.
- If bothersome dryness or peeling occurs, reduce application to once a day or every other day .

Other information

- Store away from heat and direct sunlight.
- Store at controlled room temperature: 15°C–25°C (59°F– 77°F).

Inactive ingredients

benzyl alcohol, chamomilla recutita (matricaria) flower extract, ethoxydiglycol, ext. violet 2, fragrance, glycerin, menthol, menthoxypropanediol, menthyl lactate, SD alcohol 40-B, water (aqua)

Questions or comments?

1.800.636.7546

Monday–Friday 9a.m.–4p.m. Pacific Time

Drug Facts

Active ingredient

Benzoyl peroxide 5%

Purpose

Acne treatment

Uses

- for the treatment of acne
- dries up acne pimples
- helps prevent new acne pimples

Warnings

For external use only

When using this product

- skin irritation and dryness is more likely to occur if you use another topical acne medication at the same time. If irritation occurs, only use one topical acne medication at a time
- avoid unnecessary sun exposure and use a sunscreen
- avoid contact with the eyes, lips, and mouth
- avoid contact with hair and dyed fabrics, which may be bleached by this product
- skin irritation may occur, characterized by redness, burning, itching, peeling, or possibly swelling. Irritation may be reduced by using the product less frequently or in a lower concentration.

Do not use if you

- have very sensitive skin.
- are sensitive to benzoyl peroxide.

Stop use and ask a doctor if

- irritation becomes severe.

Keep out of reach of children. If swallowed, get medical help or contact a Poison Control Center right away.

Directions

- Cleanse the skin thoroughly before applying this product.
- Cover the entire affected area with a thin layer one to three times daily.
- Because excessive drying of the skin may occur, start with one application daily, then gradually increase to two or three times daily if needed or as directed by a doctor.
- If bothersome dryness or peeling occurs, reduce application to once a day or every other day.
- If going outside, apply sunscreen after using this product. If irritation or sensitivity develops, stop use of both products and ask a doctor.

Other information

- Store away from heat and direct sunlight.
- Store at controlled room temperature: 15°C–25°C (59°F– 77°F).

Inactive ingredients

benzyl benzoate, BHT, dicaprylyl ether, dimethyl isosorbide, disodium EDTA, hydroxyethyl acrylate/sodium acryloyldimethyl taurate copolymer, phenoxyethanol, polysorbate 60, propylene glycol, squalane, water (aqua)

Questions or comments?

1.800.636.7546

Monday–Friday 9a.m.–4p.m. Pacific Time

Distributed by Obagi Cosmeceuticals LLC,
Long Beach, CA 90806

PRINCIPAL DISPLAY PANEL - Kit Carton

OBAGI®
MEDICAL

CLENZIderm M.D.® SYSTEM

Acne Therapeutic System

This CLENZIderm M.D. SYSTEM includes:

- (1) Daily Care Foaming Cleanser 4 FL. OZ. (118 mL)
- (1) Pore Therapy 5 FL. OZ. (148 mL)
- (1) Therapeutic Lotion 1.6 FL. OZ. (47 mL)